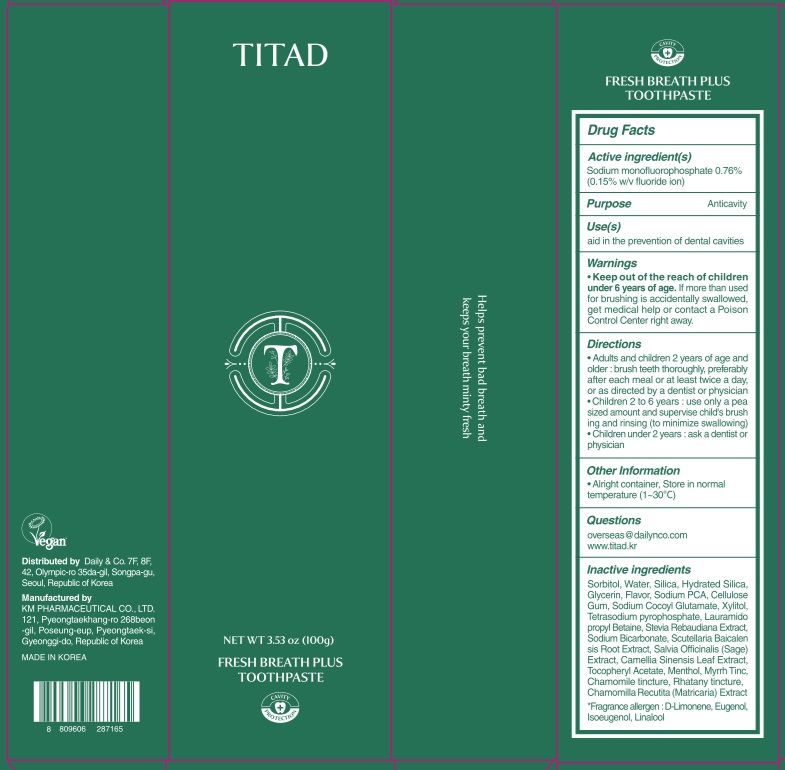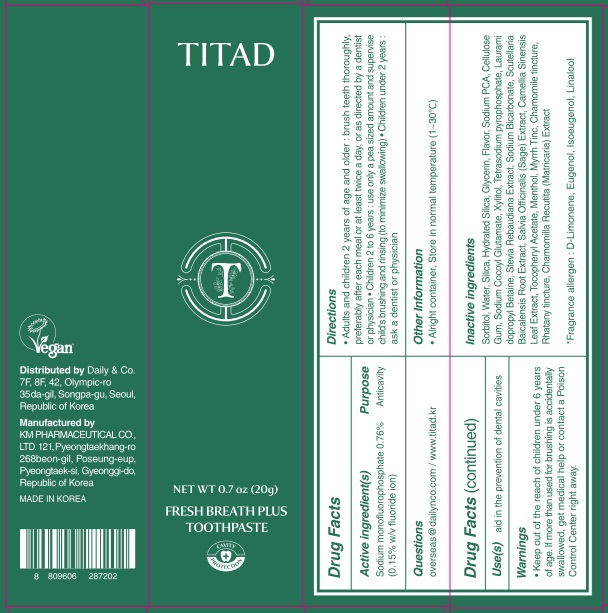 DRUG LABEL: TITAD FRESH BREATH PLUS TOOTH
NDC: 50555-200 | Form: PASTE, DENTIFRICE
Manufacturer: KMPHARMACEUTICAL CO.,LTD
Category: otc | Type: HUMAN OTC DRUG LABEL
Date: 20241216

ACTIVE INGREDIENTS: SODIUM MONOFLUOROPHOSPHATE 0.76 g/100 g
INACTIVE INGREDIENTS: XYLITOL; TETRASODIUM PYROPHOSPHATE; SORBITOL; GLYCERIN; CELLULOSE GUM; STEVIA REBAUDIANA WHOLE; CAMELLIA SINENSIS LEAF; MATRICARIA RECUTITA; LIMONENE, (+)-; WATER; SCUTELLARIA BAICALENSIS ROOT; SAGE; ISOEUGENOL; .ALPHA.-TOCOPHEROL ACETATE; SODIUM COCOYL GLUTAMATE; LAURAMIDOPROPYL BETAINE; SODIUM BICARBONATE; EUGENOL; HYDRATED SILICA; SODIUM PCA; LINALOOL; MENTHOL

Active ingredient(s)

Sodium monofluorophosphate 0.76% (0.15% w/v fluoride ion)

Inactive ingredients

Sorbitol, Water, Silica, Hydrated Silica, Glycerin, Flavor, Sodium PCA, Cellulose Gum, Sodium Cocoyl Glutamate, Xylitol, Tetrasodium pyrophosphate, Lauramidopropyl Betaine, Stevia Rebaudiana Extract, Sodium Bicarbonate, Scutellaria Baicalensis Root Extract, Salvia Officinalis (Sage) Extract, Camellia Sinensis Leaf Extract, Tocopheryl Acetate, Menthol, Myrrh Tinc, Chamomile tincture, Rhatany tincture, Chamomilla Recutita (Matricaria) Extract

Fragrance allergen : D-Limonene, Eugenol, Isoeugenol, Linalool

Purpose

Anticavity

Warnings

■ Keep out of the reach of children under 6 years of age. If more than used for brushing is accidentally swallowed, get medical help or contact a Poison Control Center right away.

Keep out of the reach of children

INDICATIONS AND USAGE

Use(s)

aid in the prevention of dental cavities

Directions

■ adults and children 2 years of age and older : brush teeth thoroughly, preferably after each meal or at least twice a day, or as directed by a dentist or physician

■ children 2 to 6 years : use only a pea sized amount and supervise child's brushing and rinsing (to minimize swallowing)

■ children under 2 years : ask a dentist or physician

Other Information

■ Alright container, Store in normal temperature (1~30℃)

Questions

overseas@dailynco.com

www.titad.kr